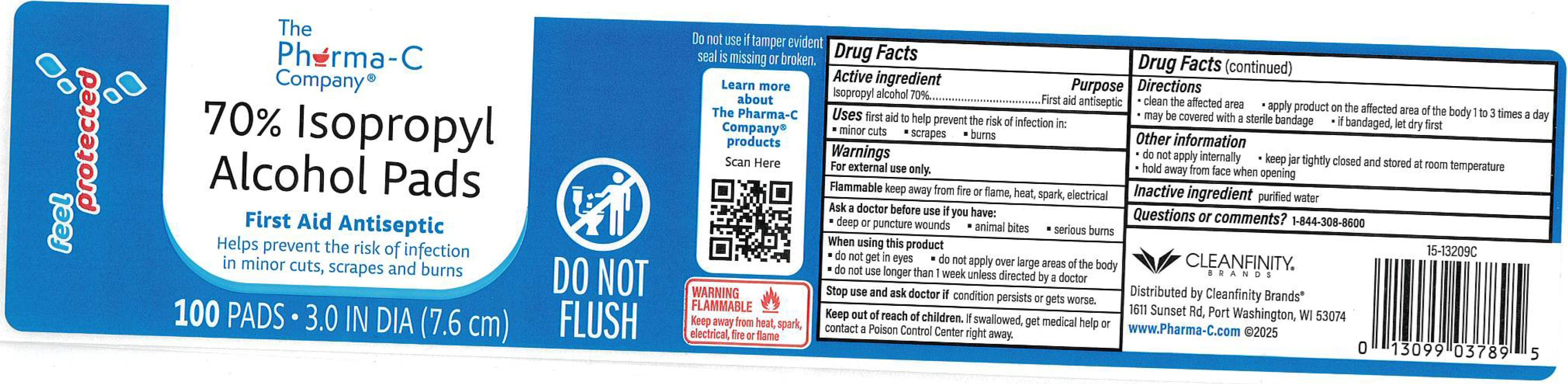 DRUG LABEL: The Pharma-C Company 70 Isopropyl Alcohol Pads
NDC: 55239-361 | Form: CLOTH
Manufacturer: Kleen Test Products Corporation
Category: otc | Type: HUMAN OTC DRUG LABEL
Date: 20251209

ACTIVE INGREDIENTS: ISOPROPYL ALCOHOL 70 mL/100 mL
INACTIVE INGREDIENTS: WATER

The Pharma-C Company 70% Isopropyl Alcohol Pads

Active ingredient

Isopropyl alcohol 70%

Purpose

First aid antiseptic

Uses

first aid to help prevent the risk of infection in:

• minor cuts • scrapes • burns

Warnings

For external use only.

Flammablekeep away from fire or flame, heat, spark, electrical

Ask a doctor before use if you have

• deep or puncture wounds • animal bites • serious burns

When using this product

• do not get in eyes • do not apply over large areas of the body • do not use longer than 1 week unless directed by a doctor

Stop use and ask doctor

if condition persists or gets worse.

Keep out of reach of children.

If swallowed, get medical help or contact a Poison Control Center right away.

Directions

• clean the affected area • apply product on the affected area of the body 1 to 3 times a day • may be covered with a sterile bandage • if bandaged, let dry first

Other information

• do not apply internally • keep jar tightly closed and stored at room temperature • hold away from face when opening

Inactive ingredients

purified water

Questions or comments?

1-844-308-8600